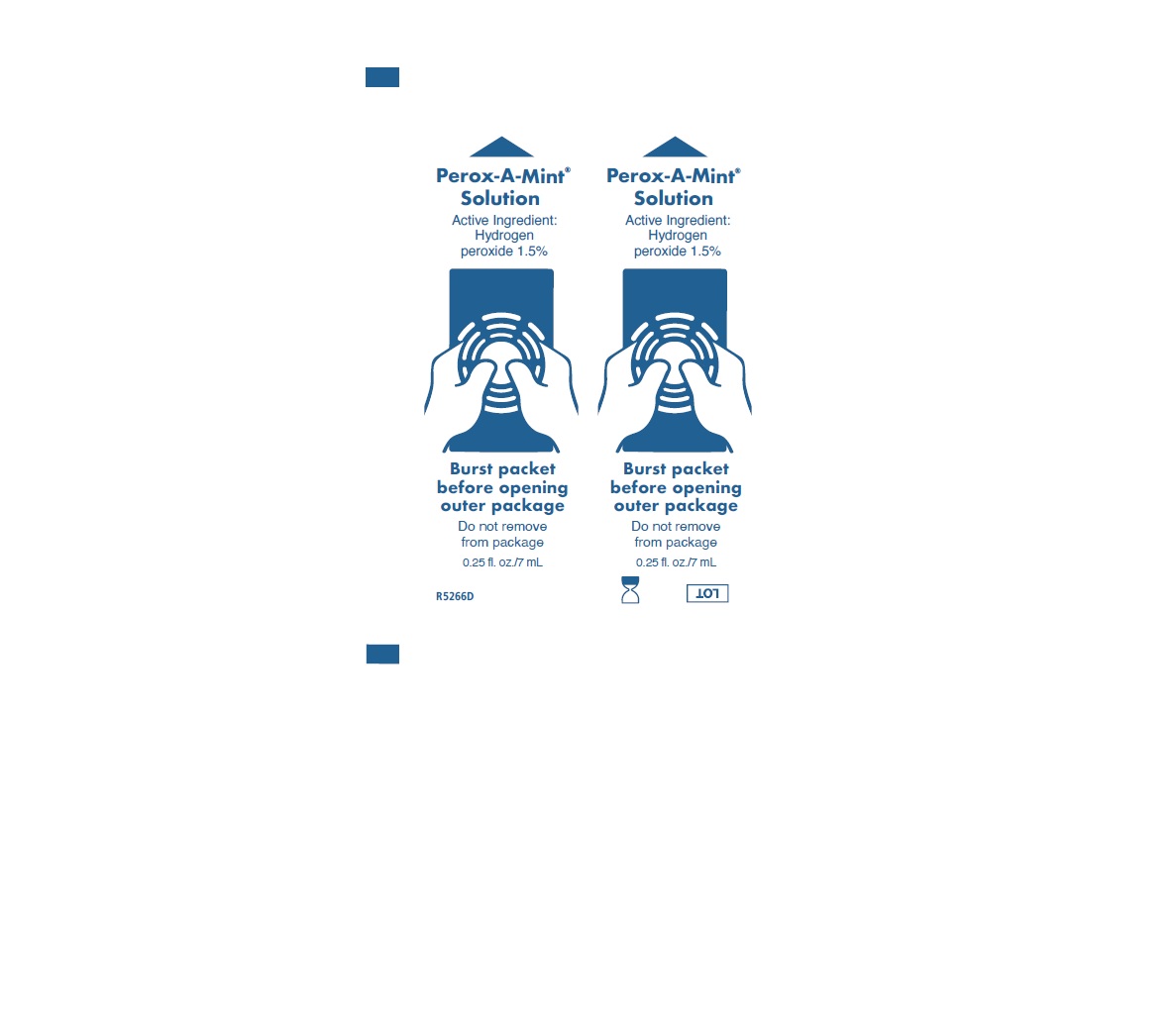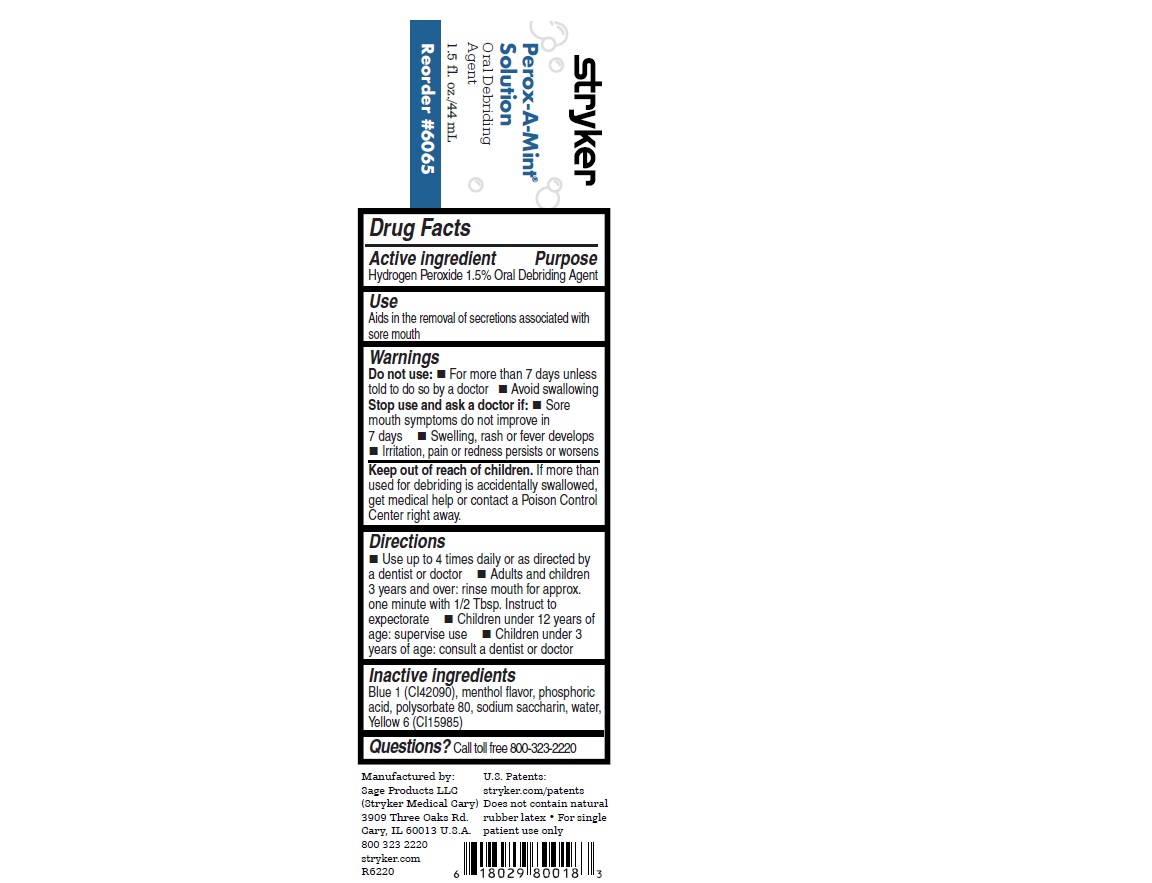 DRUG LABEL: Perox-A-Mint Solution
NDC: 53462-075 | Form: MOUTHWASH
Manufacturer: Sage Products, LLC
Category: otc | Type: HUMAN OTC DRUG LABEL
Date: 20251208

ACTIVE INGREDIENTS: HYDROGEN PEROXIDE 15 mg/1 mL
INACTIVE INGREDIENTS: WATER; PHOSPHORIC ACID; POLYSORBATE 80; SACCHARIN SODIUM; FD&C BLUE NO. 1; FD&C YELLOW NO. 6

Perox-A-Mint® Solution

Active ingredient

Hydrogen Peroxide 1.5%

Purpose

Oral Debriding Agent

Use

Aids in the removal of secretions associated with sore mouth

Warnings

Do not use:

- For more than 7 days unless told to do so by a doctor.
- Avoid swallowing.

Stop use and ask a doctor if:

- Sore mouth symptoms do not improve in 7 days.
- Swelling, rash or fever develops.
- Irritation, pain or redness persists of worsens.

Keep out of reach of children. If more than used for debriding is accidentally swallowed, get medical help or contact a Poison Control Center right away.

Directions

- Use up to 4 times daily or as directed by a dentist or doctor.
- Adults and children 3 years and over: rinse mouth for approx. one minute with 1/2 Tbsp. Instruct to expectorate.
- Children under 12 years of age: supervise use.
- Children under 3 years of age: consult a dentist or doctor.

Inactive Ingredients

Blue 1 (CI42090), menthol flavor, phosphoric acid, polysorbate 80, sodium saccharin, Water, Yellow 6 (CI15985)

Questions?Call toll free 800-323-2220